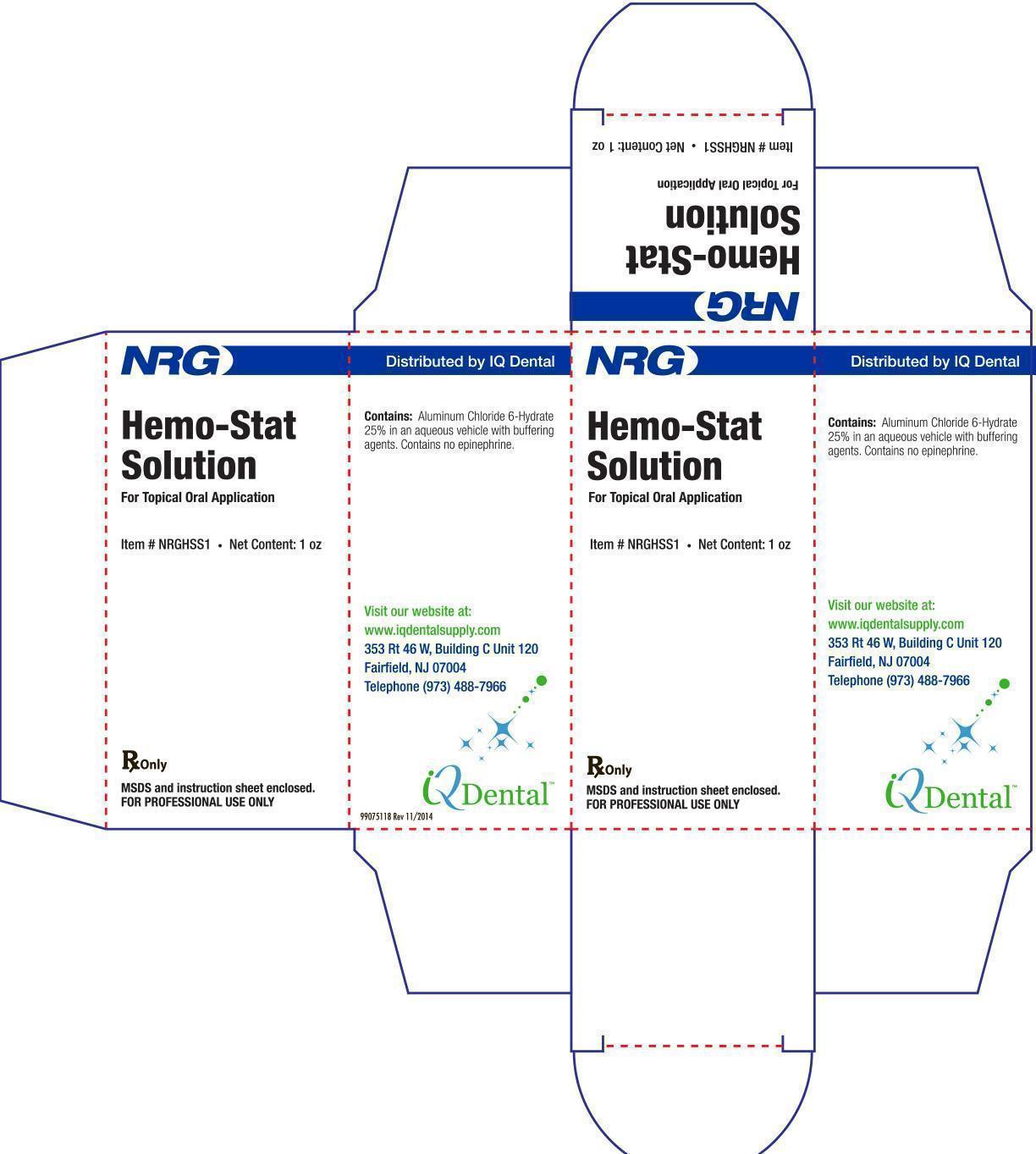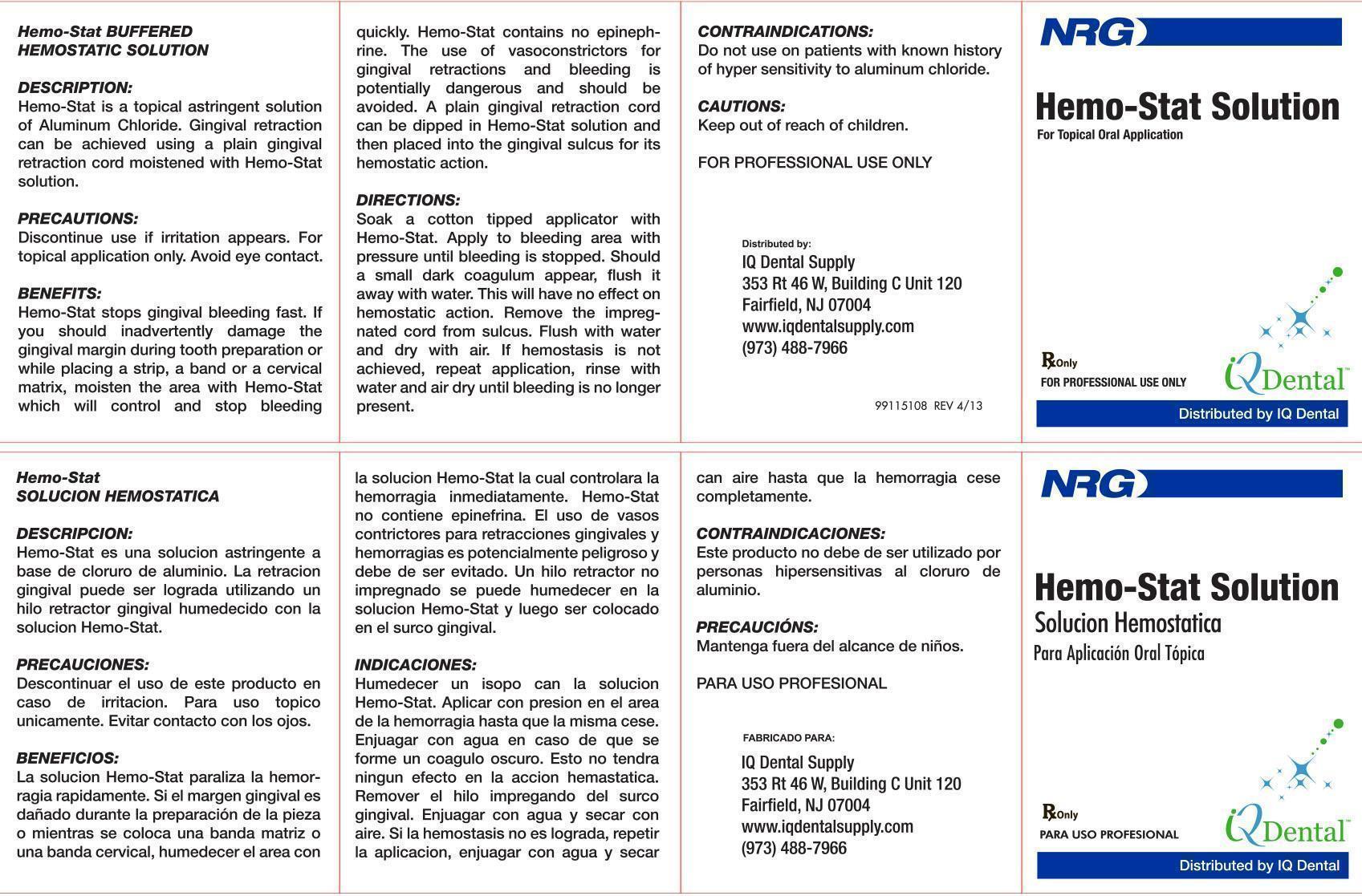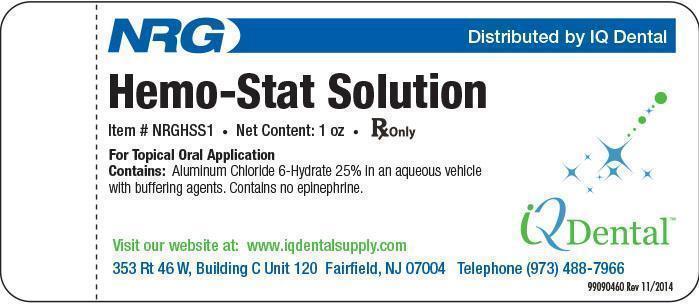 DRUG LABEL: NRG Hemo-Stat
NDC: 42756-1100 | Form: SOLUTION
Manufacturer: IQ Dental Supply, LLC
Category: prescription | Type: HUMAN PRESCRIPTION DRUG LABEL
Date: 20220127

ACTIVE INGREDIENTS: ALUMINUM CHLORIDE 7500 mg/30 mL
INACTIVE INGREDIENTS: WATER; PROPYLENE GLYCOL; POTASSIUM CHLORIDE; DMDM HYDANTOIN

DESCRIPTION:

Hemo-Stat is a topical astringent solution of Aluminum Chloride. Gingival retraction can be achieved using a plain gingival retraction cord moistened with Hemo-Stat solution.

PRECAUTIONS:

Discontinue use if irritation appears. For topical application only. Avoid eye contact.

BENEFITS:

Hemo-Stat stops gingival bleeding fast. If you should inadvertantly damage the gingival margin during tooth preparation or while placing a strip, a band or a cervical matrix, moisten the area with Hemo-Stat which will control and stop bleeding quickly. Hemo-Stat contains no epinephrine. The use of vasoconstrictors for gingival retractions and bleeding is potentially dangerous and should be avoided. A plain gingival retraction cord can be dipped in Hemo-Stat solution and then placed into the gingival sulcus for its hemostatic action.

DIRECTIONS:

Soak a cotton tipped applicator with Hemo-Stat. Apply to bleeding area with pressure until bleeding is stopped. Should a small dark coagulum appear, flush it away with water. This will have no effect on hemostatic action. Remove the impregnated cord from sulcus. Flush with water and dry with air. If hemostasis is not achieved, repeat application, rinse with water and air dry until bleeding is no longer present.

CONTRAINDICATIONS:

Do not use in patients with a known history of hypersensitivity to aluminum chloride.

CAUTION:

Keep out of reach of children.

FOR PROFESSIONAL USE ONLY.